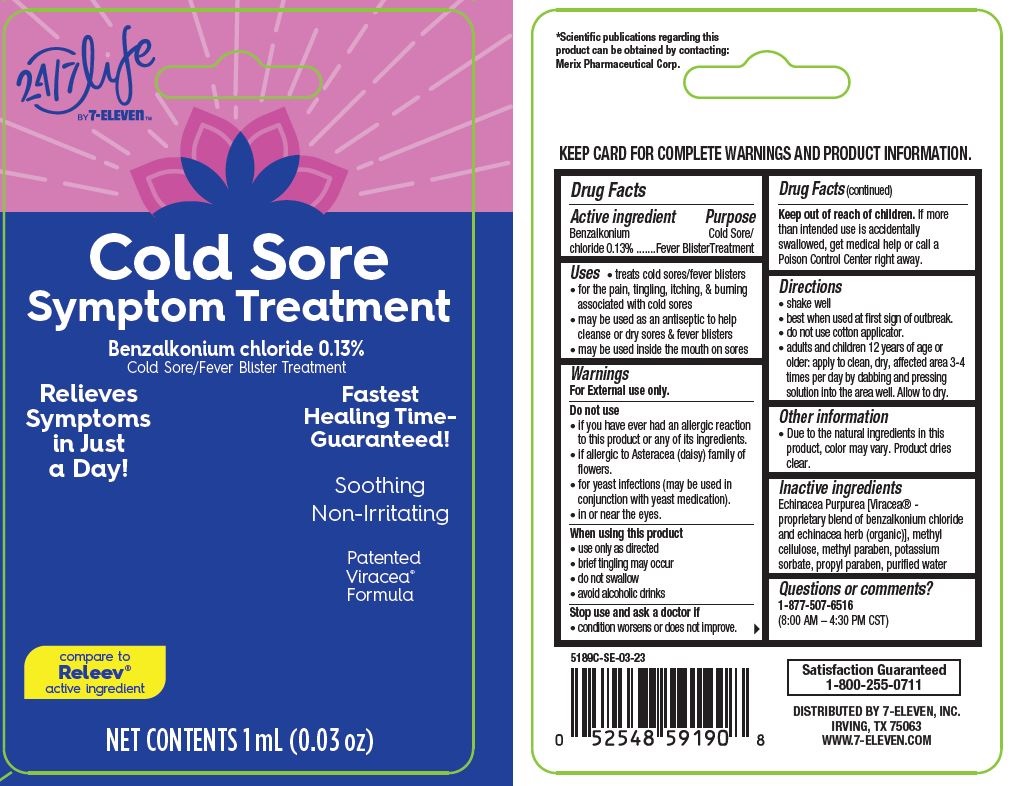 DRUG LABEL: Cold Sore Treatment, 24-7 Life by 7-Eleven
NDC: 66715-5189 | Form: LIQUID
Manufacturer: Lil' Drug Store Products, Inc.
Category: otc | Type: HUMAN OTC DRUG LABEL
Date: 20240119

ACTIVE INGREDIENTS: BENZALKONIUM CHLORIDE 1.3 mg/1 mL
INACTIVE INGREDIENTS: POTASSIUM SORBATE; WATER; METHYLPARABEN; PROPYLPARABEN; METHYLCELLULOSE, UNSPECIFIED; ECHINACEA PURPUREA FLOWERING TOP

Cold Sore Treatment, 24/7 Life by 7-Eleven

Drug Facts

Active ingredient

Benzalkonium chloride 0.13%

Purpose

Cold Sore/Fever BlisterTreatment

Uses

- treats cold sores/fever blisters
- for the pain, tingling, itching, & burning associated with cold sores
- may be used as an antiseptic to help cleanse or dry sores & fever blisters
- may be used inside the mouth on sores

Warnings

For External use only.

Do not use

- if you have ever had an allergic reaction to this product or any of its ingredients.
- if allergic to Asteracea (daisy) family of flowers.
- for yeast infections (may be used in conjunction with yeast medication).
- in or near the eyes.

When using this product

- use only as directed
- brief tingling may occur
- do not swallow
- avoid alcoholic drinks

Stop use and ask a doctor if

- condition worsens or does not improve.

Keep out of reach of children. If more than intended use is accidentally swallowed, get medical help or call a
Poison Control Center right away.

Directions

- shake well
- best when used at first sign of outbreak.
- do not use cotton applicator.
- adults and children 12 years of age or older: apply to clean, dry, affected area 3-4 times per day by dabbing and pressing solution into the area well. Allow to dry.

Other information

- Due to the natural ingredients in this product, color may vary. Product dries clear.

Inactive ingredients

Echinacea Purpurea [Viracea® - proprietary blend of benzalkonium chloride and echinacea herb (organic)], methyl cellulose, methyl paraben, potassium sorbate, propyl paraben, purified water

Questions or comments?

1-877-507-6516 (8:00 AM – 4:30 PM CST)

Cold Sore Treatment, 24/7 by 7-ElevenTM - PDP/Package

24/7 Life by 7-ElevenTM

Cold Sore

Symptom Treatment

Benzalkonium chloride 0.13%

Cold Sore/Fever Blister Treatment

Relieves
Symptoms
in Just
a Day!

Fastest
Healing Time-
Guaranteed!

Soothing
Non-Irritating
Patented
Viracea®
Formula

compare to
Releev®
active ingredient

NET CONTENTS 1 mL (0.03 oz)